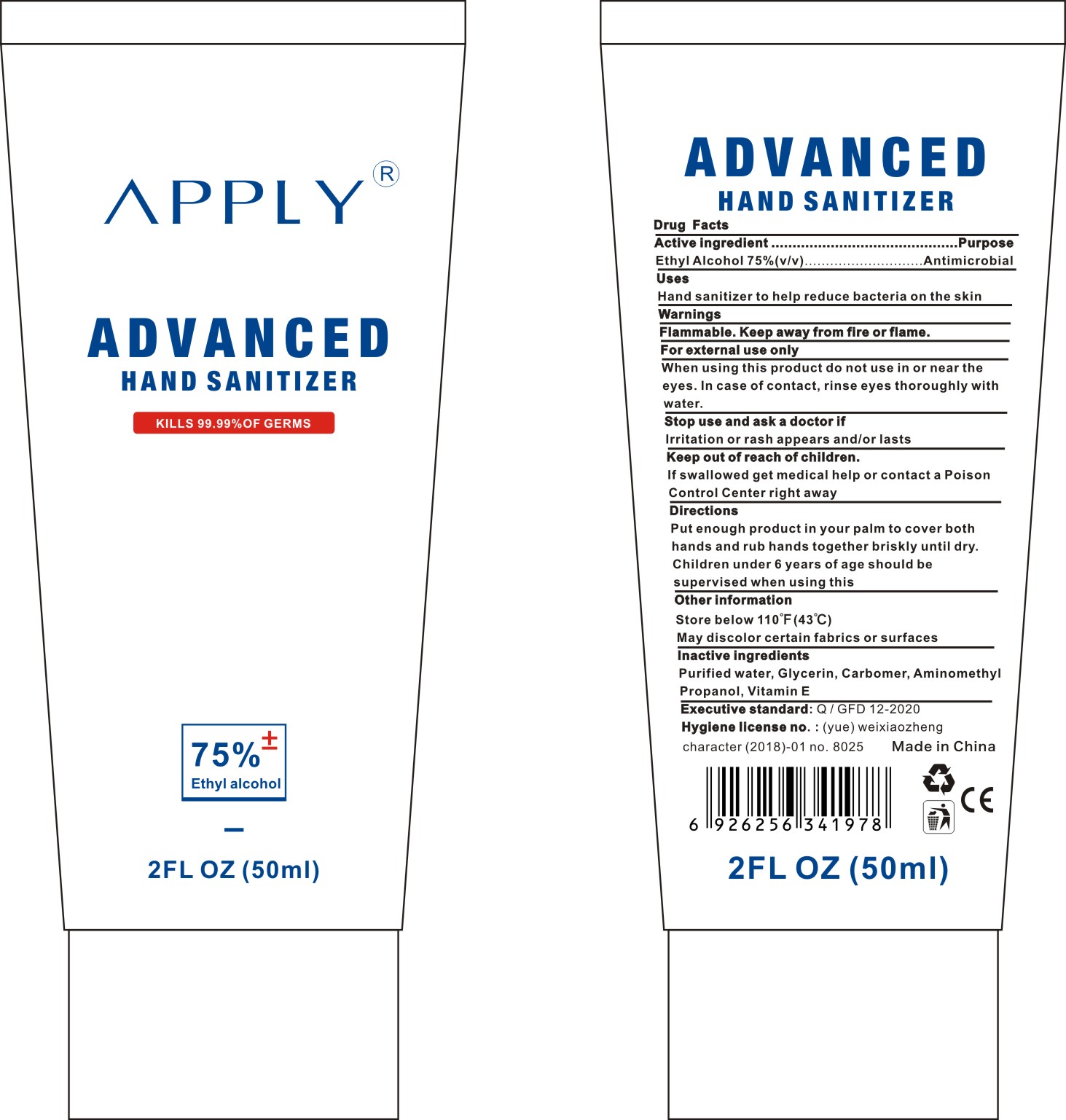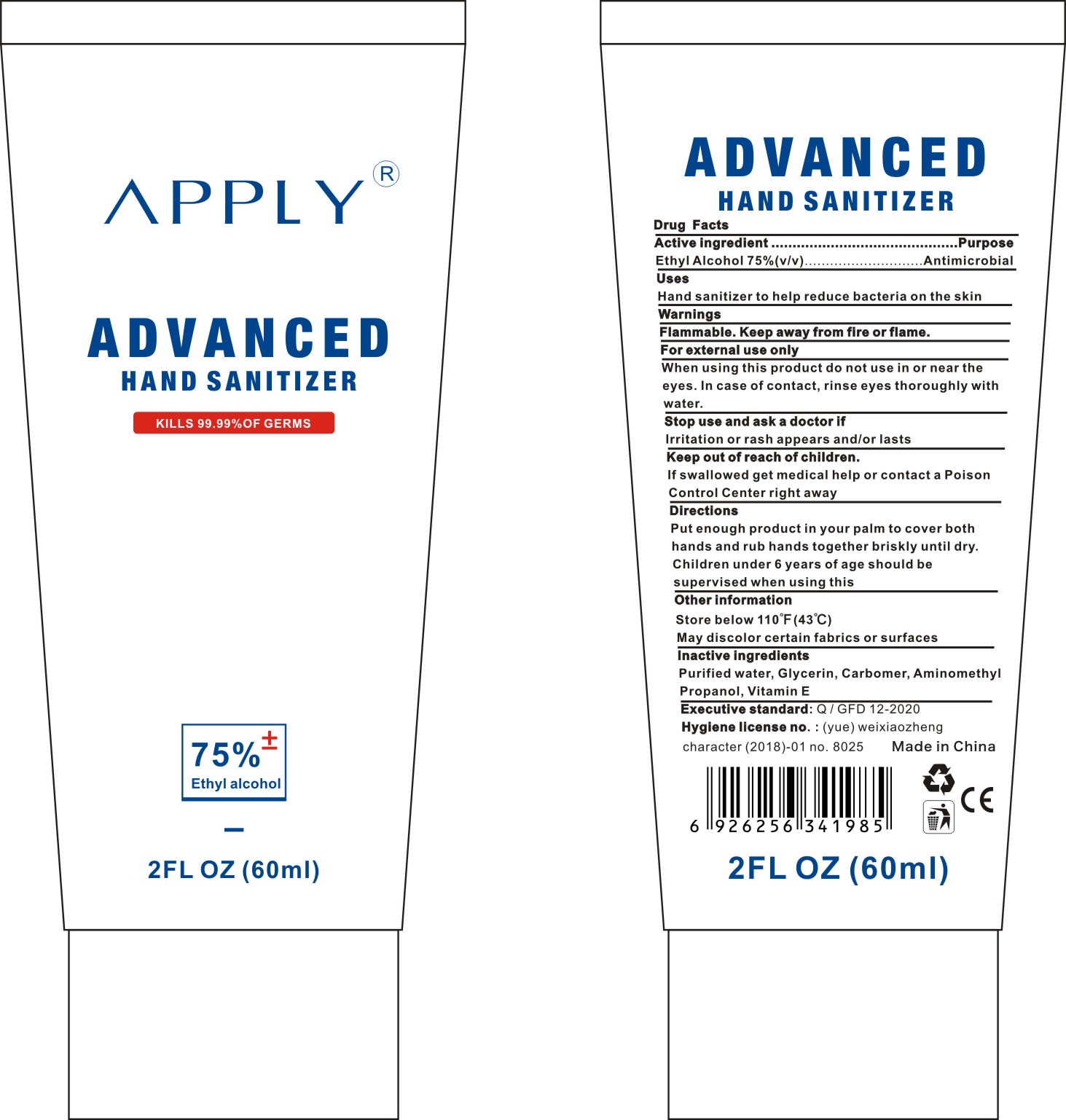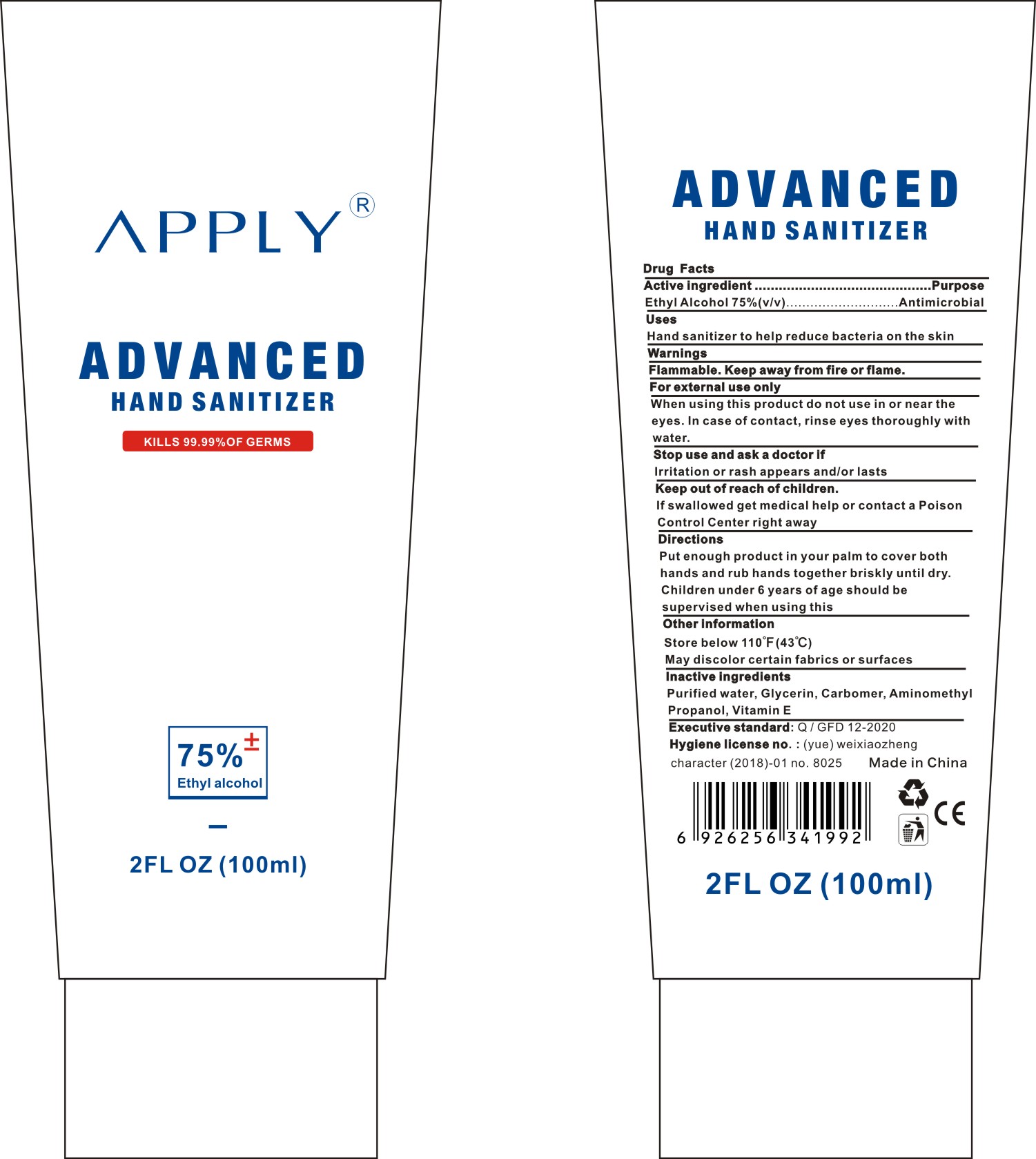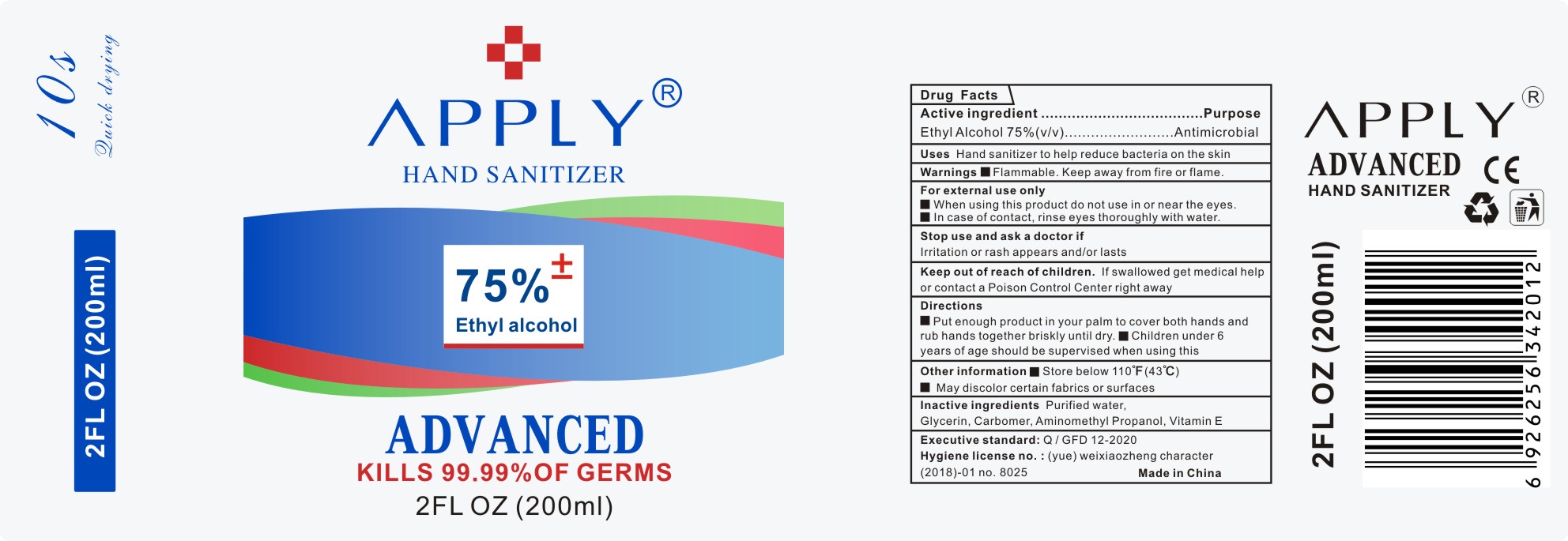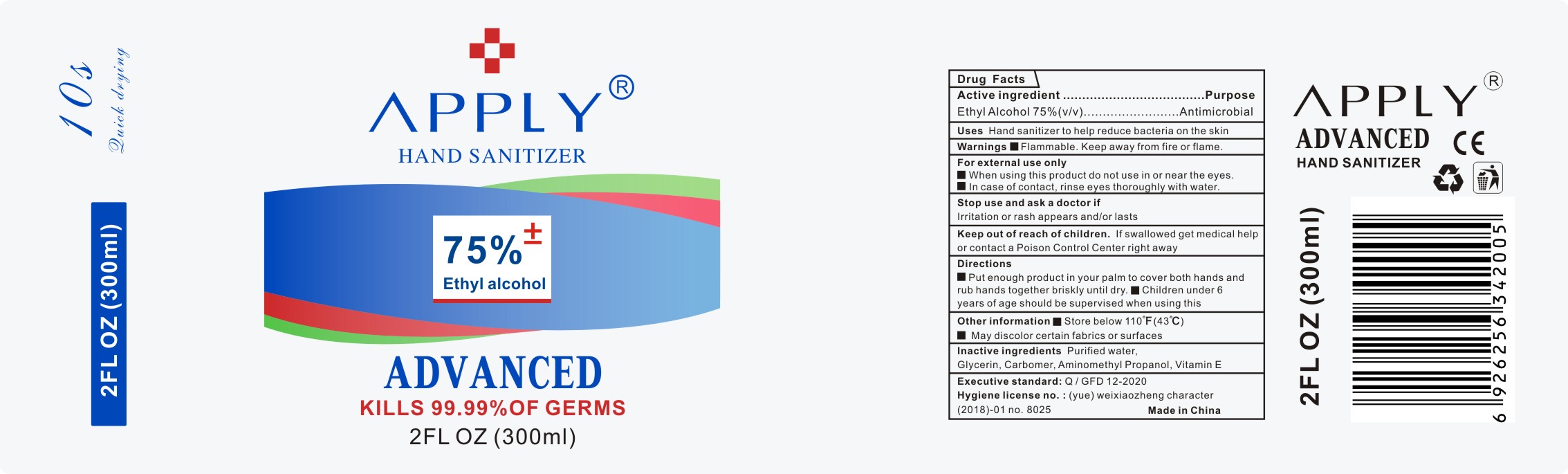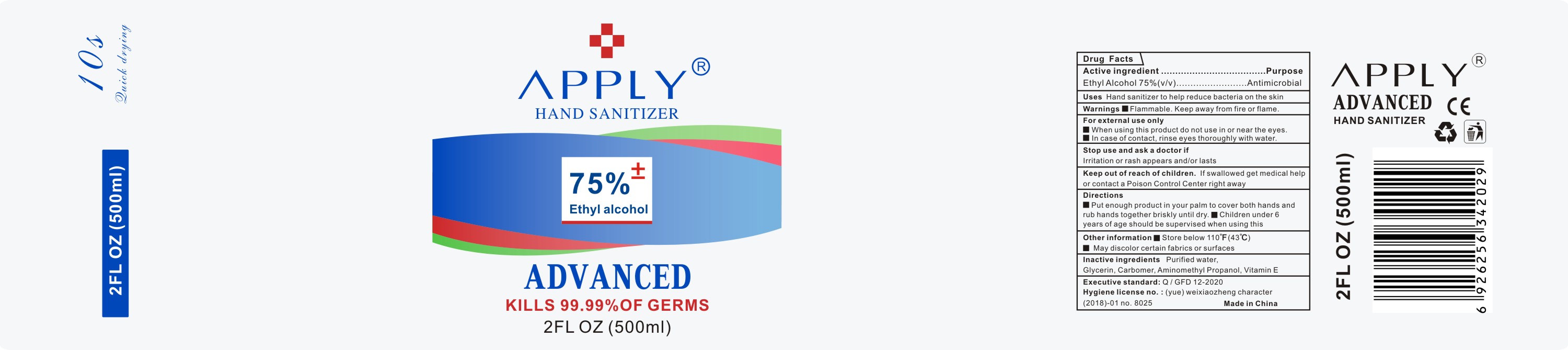 DRUG LABEL: advanced hand sanitizer
NDC: 75151-001 | Form: GEL
Manufacturer: Guangzhou Fuda Biotechnology Co., Ltd.
Category: otc | Type: HUMAN OTC DRUG LABEL
Date: 20200420

ACTIVE INGREDIENTS: ALCOHOL 75 mL/100 mL
INACTIVE INGREDIENTS: GLYCERIN; AMINOMETHYLPROPANOL; .ALPHA.-TOCOPHEROL; WATER; CARBOMER HOMOPOLYMER, UNSPECIFIED TYPE

ADVANCED HAND SANITIZER

Active ingredient

Ethyl Alcohol 75%(v/v)

Purpose

Antimicrobial

Uses

Hand sanitizer to help reduce bacteria on the skin.

Warnings

Flammable.Keep away from fire or flame.For external use only

When using this product

do not use in or near the eyes.In case of contact,rinse eyes thoroughly with water.

Stop use and ask a doctor if Irritation or rash appears and/or lasts

Keep out of reach of children

If swallowed get medical help or contact a Poison Control Center right away

Directions

Put enough product in your palm to cover both hands and rub hands together briskly until dry.

Children under 6 years of age should be supervised when using this.

Other information

Store below 110°F(43℃)

May discolor certain fabrics or surfaces

Inactive ingredients

Purified water, Glycerin,Carbomer,Aminomethyl Propanol, Vitamin E